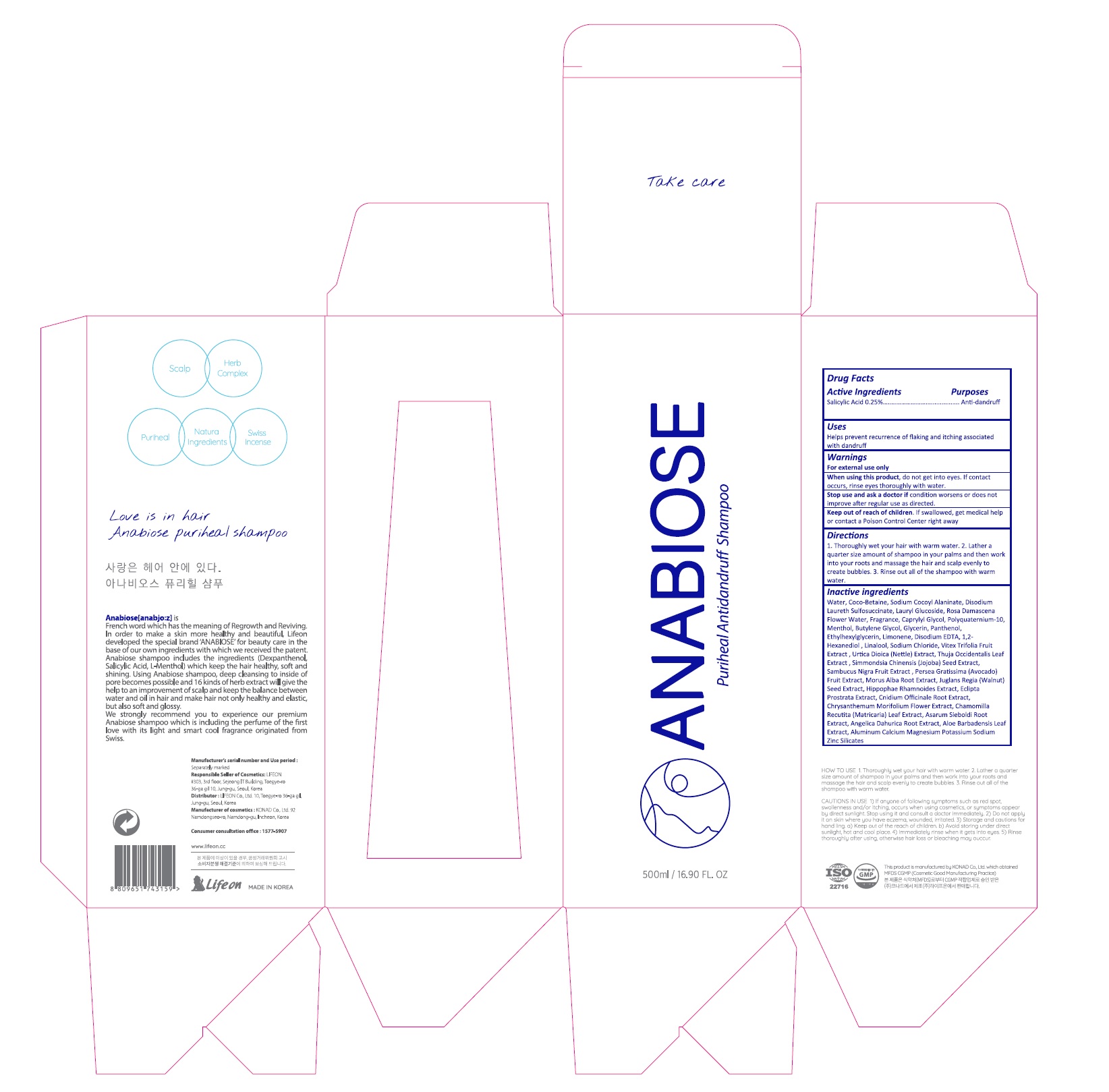 DRUG LABEL: ANABIOSE PURIHEAL
NDC: 70602-009 | Form: SHAMPOO
Manufacturer: LIFEON Corp.
Category: otc | Type: HUMAN OTC DRUG LABEL
Date: 20220712

ACTIVE INGREDIENTS: SALICYLIC ACID 2.5 g/100 mL
INACTIVE INGREDIENTS: WATER; COCO-BETAINE; DISODIUM LAURETH SULFOSUCCINATE; LAURYL GLUCOSIDE; ROSA X DAMASCENA FLOWER OIL; CAPRYLYL GLYCOL; POLYQUATERNIUM-10 (1000 MPA.S AT 2%); MENTHOL, UNSPECIFIED FORM; BUTYLENE GLYCOL; GLYCERIN; PANTHENOL; ETHYLHEXYLGLYCERIN; LIMONENE, (-)-; EDETATE DISODIUM ANHYDROUS; 1,2-HEXANEDIOL; SIMMONDSIA CHINENSIS SEED; EUROPEAN ELDERBERRY; AVOCADO; MORUS ALBA ROOT; ENGLISH WALNUT; HIPPOPHAE RHAMNOIDES FRUIT; ECLIPTA PROSTRATA LEAF; CNIDIUM OFFICINALE ROOT; CHRYSANTHEMUM X MORIFOLIUM FLOWER; MATRICARIA CHAMOMILLA LEAF; ASARUM SIEBOLDII ROOT; ANGELICA DAHURICA ROOT; ALOE VERA LEAF; LINALOOL, (+/-)-; SODIUM CHLORIDE; VITEX TRIFOLIA FRUIT; URTICA DIOICA LEAF; THUJA OCCIDENTALIS LEAF

70602-009_ANABIOSE PURIHEAL SHAMPOO

ACTIVE INGREDIENT

Salicylic Acid 0.25%

INACTIVE INGREDIENT

Water, Coco-Betaine, Sodium Cocoyl Alaninate, Disodium Laureth Sulfosuccinate, Lauryl Glucoside, Rosa Damascena Flower Water, Fragrance, Caprylyl Glycol, Polyquaternium-10, Menthol, Butylene Glycol, Glycerin, Panthenol, Ethylhexylglycerin, Limonene, Disodium EDTA, 1,2-Hexanediol , Linalool, Sodium Chloride, Vitex Trifolia Fruit Extract , Urtica Dioica (Nettle) Extract, Thuja Occidentalis Leaf Extract , Simmondsia Chinensis (Jojoba) Seed Extract, Sambucus Nigra Fruit Extract , Persea Gratissima (Avocado) Fruit Extract, Morus Alba Root Extract, Juglans Regia (Walnut) Seed Extract, Hippophae Rhamnoides Extract, Eclipta Prostrata Extract, Cnidium Officinale Root Extract, Chrysanthemum Morifolium Flower Extract, Chamomilla Recutita (Matricaria) Leaf Extract, Asarum Sieboldi Root Extract, Angelica Dahurica Root Extract, Aloe Barbadensis Leaf Extract, Aluminum Calcium Magnesium Potassium Sodium Zinc Silicates

PURPOSE

Anti-dandruff

keep out or reach of the children

INDICATIONS AND USAGE

Helps prevent recurrence of flaking and itching associated with dandruff

WARNINGS

For external use only.

When using this product, do not get into eyes. If contact occurs, rinse eyes thoroughly with water.

Stop use and ask a doctor if condition worsens or does not improve after regular use as directed.

DOSAGE AND ADMINISTRATION

1. Thoroughly wet your hair with warm water. 2. Lather a quarter size amount of shampoo in your palms and then work into your roots and massage the hair and scalp evenly to create bubbles. 3. Rinse out all of the shampoo with warm water.